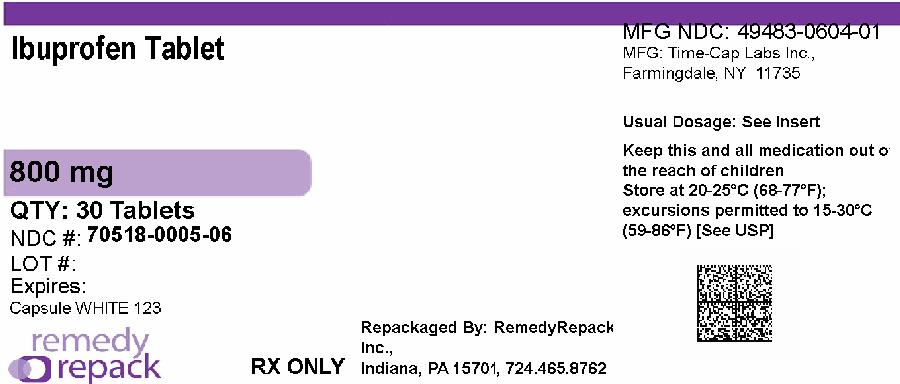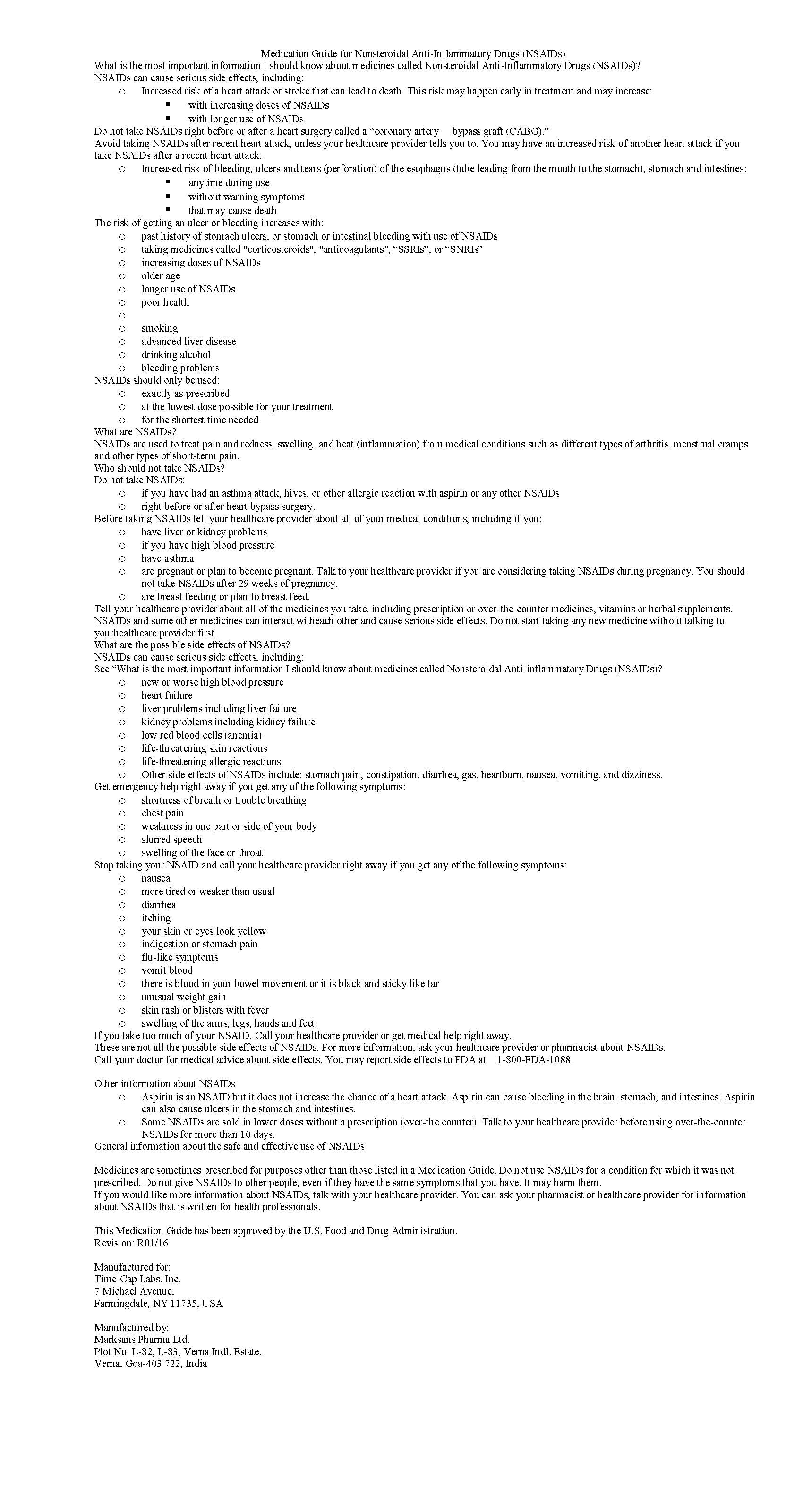 DRUG LABEL: IBUPROFEN
NDC: 70518-0005 | Form: TABLET, FILM COATED
Manufacturer: REMEDYREPACK INC.
Category: prescription | Type: HUMAN PRESCRIPTION DRUG LABEL
Date: 20260107

ACTIVE INGREDIENTS: IBUPROFEN 800 mg/1 1
INACTIVE INGREDIENTS: CROSCARMELLOSE SODIUM; MAGNESIUM STEARATE; CELLULOSE, MICROCRYSTALLINE; POLYETHYLENE GLYCOL, UNSPECIFIED; POLYVINYL ALCOHOL; STARCH, PREGELATINIZED CORN; TALC; TITANIUM DIOXIDE; SILICON DIOXIDE

IBUPROFEN 400 MG - 600 MG AND 800 MG TABLETS

ibuprofen tablets 400 mg - 600 mg- 800 mg medguide

Repackaged By / Distributed By: RemedyRepack Inc.

625 Kolter Drive, Indiana, PA 15701

(724) 465-8762

HOW SUPPLIED

600mg (white to off white, capsule shaped, biconvex, film coated tablets debossed with '122' on one side and plain on the other side) Bottles of 30, 50, 100 & 500

HOW SUPPLIED

Ibuprofen tablets are available in the following strength:

800 mg (white to off white, capsule shaped, biconvex, film coated tablets debossed with ‘123’ on one side and plain on other side)

NDC: 70518-0005-00

NDC: 70518-0005-01

NDC: 70518-0005-02

NDC: 70518-0005-03

NDC: 70518-0005-04

NDC: 70518-0005-05

NDC: 70518-0005-06

PACKAGING: 21 in 1 BLISTER PACK

PACKAGING: 14 in 1 BLISTER PACK

PACKAGING: 30 in 1 BLISTER PACK

PACKAGING: 10 in 1 BLISTER PACK

PACKAGING: 90 in 1 BOTTLE PLASTIC

PACKAGING: 30 in 1 BOTTLE PLASTIC

PACKAGING: 30 in 1 BLISTER PACK

“Preserve in well-closed containers”

Store at 20 ° to 25°C (68°to 77°F) [See USP Controlled Room Temperature].

Rx only

Repackaged and Distributed By:

Remedy Repack, Inc.

625 Kolter Dr. Suite #4 Indiana, PA 1-724-465-8762

HOW SUPPLIED

Ibuprofen tablets are available in the following strength:

800 mg (white to off white, capsule shaped, biconvex, film coated tablets debossed with ‘123’ on one side and plain on other side)

NDC: 70518-0005-00

NDC: 70518-0005-01

NDC: 70518-0005-02

NDC: 70518-0005-03

NDC: 70518-0005-04

NDC: 70518-0005-05

NDC: 70518-0005-06

PACKAGING: 21 in 1 BLISTER PACK

PACKAGING: 14 in 1 BLISTER PACK

PACKAGING: 30 in 1 BLISTER PACK

PACKAGING: 10 in 1 BLISTER PACK

PACKAGING: 90 in 1 BOTTLE PLASTIC

PACKAGING: 30 in 1 BOTTLE PLASTIC

PACKAGING: 30 in 1 BLISTER PACK

“Preserve in well-closed containers”

Store at 20 ° to 25°C (68°to 77°F) [See USP Controlled Room Temperature].

Rx only

Repackaged and Distributed By:

Remedy Repack, Inc.

625 Kolter Dr. Suite #4 Indiana, PA 1-724-465-8762

PRINCIPAL DISPLAY PANEL

DRUG: IBUPROFEN

GENERIC: IBUPROFEN

DOSAGE: TABLET, FILM COATED

ADMINSTRATION: ORAL

NDC: 70518-0005-0

NDC: 70518-0005-1

NDC: 70518-0005-2

NDC: 70518-0005-3

NDC: 70518-0005-4

NDC: 70518-0005-5

NDC: 70518-0005-6

COLOR: white

SHAPE: CAPSULE

SCORE: No score

SIZE: 19 mm

IMPRINT: 123

PACKAGING: 21 in 1 BLISTER PACK

PACKAGING: 14 in 1 BLISTER PACK

PACKAGING: 30 in 1 BLISTER PACK

PACKAGING: 10 in 1 BLISTER PACK

PACKAGING: 90 in 1 BOTTLE PLASTIC

PACKAGING: 30 in 1 BOTTLE PLASTIC

PACKAGING: 30 in 1 BLISTER PACK

ACTIVE INGREDIENT(S):

- IBUPROFEN 800mg in 1

INACTIVE INGREDIENT(S):

- SILICON DIOXIDE
- CROSCARMELLOSE SODIUM
- MAGNESIUM STEARATE
- CELLULOSE, MICROCRYSTALLINE
- POLYETHYLENE GLYCOL, UNSPECIFIED
- POLYVINYL ALCOHOL
- STARCH, PREGELATINIZED CORN
- TALC
- TITANIUM DIOXIDE